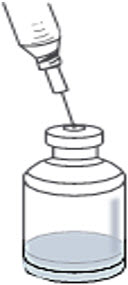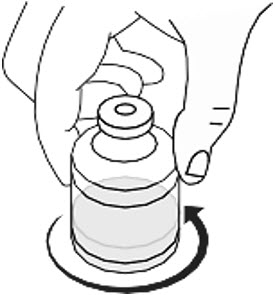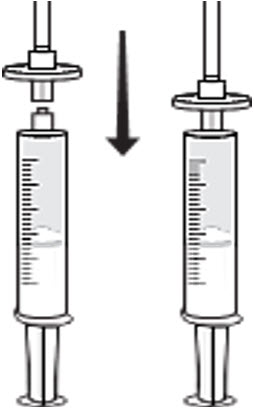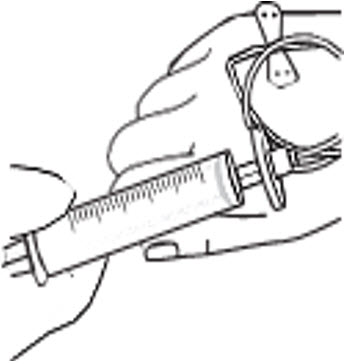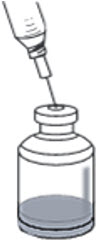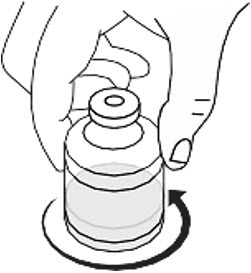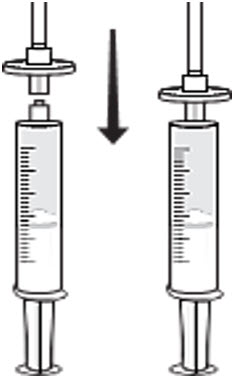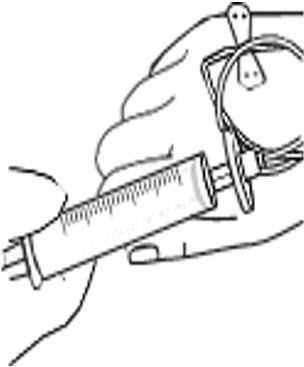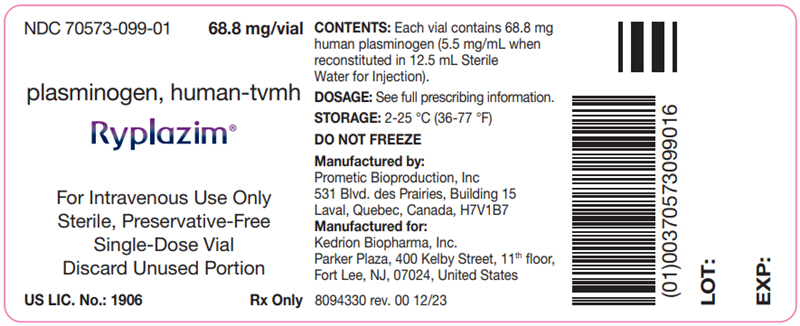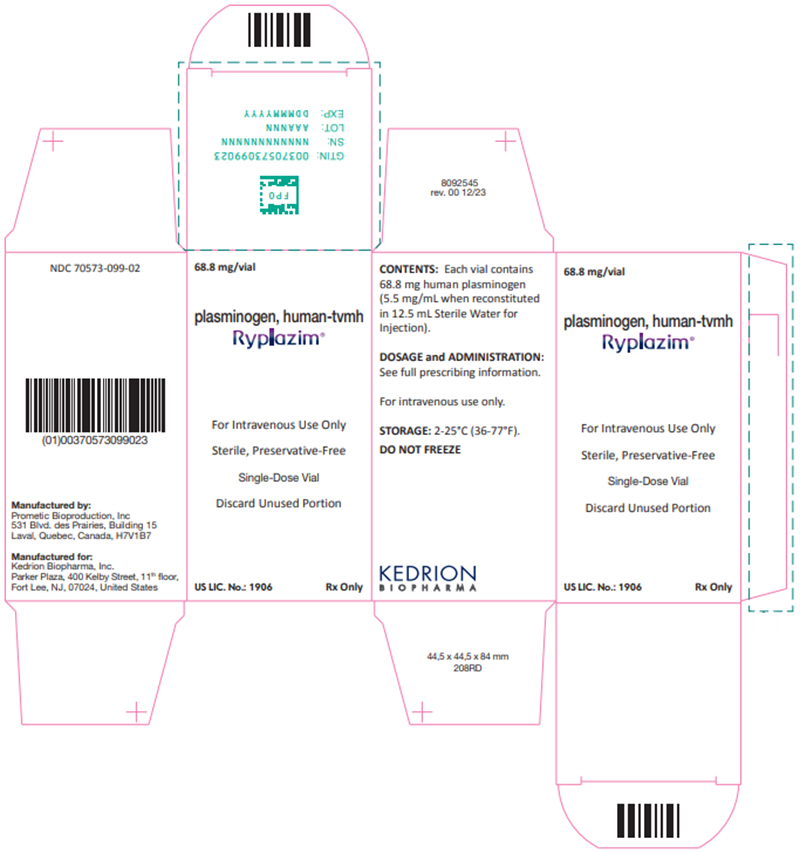 DRUG LABEL: Ryplazim
NDC: 70573-099 | Form: INJECTION, POWDER, LYOPHILIZED, FOR SOLUTION
Manufacturer: Kedrion Biopharma, Inc.
Category: other | Type: PLASMA DERIVATIVE
Date: 20250915

ACTIVE INGREDIENTS: PLASMINOGEN 68.8 mg/1 1
INACTIVE INGREDIENTS: SUCROSE; GLYCINE; SODIUM CITRATE, UNSPECIFIED FORM; SODIUM CHLORIDE

HIGHLIGHTS OF PRESCRIBING INFORMATION

These highlights do not include all the information needed to use RYPLAZIM® safely and effectively. See full prescribing information for RYPLAZIM.
RYPLAZIM® (plasminogen, human-tvmh)
lyophilized powder for reconstitution, for intravenous use
Initial U.S. Approval: 2021

1 INDICATIONS AND USAGE

RYPLAZIM® (plasminogen, human-tvmh) is plasma-derived human plasminogen indicated for the treatment of patients with plasminogen deficiency type 1 (hypoplasminogenemia). (1)

2 DOSAGE AND ADMINISTRATION

For intravenous use after reconstitution only.

The recommended dosage of RYPLAZIM is 6.6 mg/kg body weight given every 2 to 4 days. (2.1)

3 DOSAGE FORMS AND STRENGTHS

RYPLAZIM is available in a single-dose 50-mL vial containing 68.8 mg of plasminogen as a lyophilized powder for reconstitution with 12.5 mL of Sterile Water for Injection, USP (SWFI). After reconstitution, each vial will contain 5.5 mg/mL of plasminogen. (3)

4 CONTRAINDICATIONS

RYPLAZIM is contraindicated in patients with known hypersensitivity to plasminogen, or other components of RYPLAZIM. (4) (11)

5 WARNINGS AND PRECAUTIONS

- Bleeding: RYPLAZIM administration may lead to bleeding at lesion sites or worsen active bleeding. Discontinue RYPLAZIM if serious bleeding occurs. Monitor patients during and for 4 hours after infusion when administering RYPLAZIM to patients with bleeding diatheses and patients taking anticoagulants, antiplatelet drugs, and other agents which may interfere with normal coagulation. (5.1)
- Tissue Sloughing: Respiratory distress due to tissue sloughing may occur in patients with mucosal lesions in the tracheobronchial tree following RYPLAZIM administration. Please monitor appropriately. (5.2)
- Transmission of Infectious Agents: RYPLAZIM is made from human blood and therefore carries a risk of transmitting infectious agents, e.g., viruses, the variant Creutzfeldt-Jakob disease (vCJD) agent, and theoretically, the Creutzfeldt-Jakob Disease (CJD) agent. (5.3)
- Hypersensitivity Reactions: Hypersensitivity reactions, including anaphylaxis, may occur with RYPLAZIM. If symptoms occur, discontinue RYPLAZIM and administer appropriate treatment. (5.4)
- Neutralizing Antibodies: Neutralizing antibodies (inhibitors) may develop, although were not observed in clinical trials. If clinical efficacy is not maintained (e.g., development of new or recurrent lesions), then determine plasminogen activity levels in plasma. (5.5)
- Laboratory Abnormalities: Patients receiving RYPLAZIM may have elevated blood levels of D-dimer. D-dimer levels will lack interpretability in patients being screened for venous thromboembolism (VTE). (5.6)

6 ADVERSE REACTIONS

The most frequent (incidence ≥ 10%) adverse reactions in clinical trials were abdominal pain, bloating, nausea, fatigue, extremity pain, hemorrhage, constipation, dry mouth, headache, dizziness, arthralgia, and back pain. (6)

To report SUSPECTED ADVERSE REACTIONS, contact Kedrion Biopharma, Inc. at 1-855-3KDRION (1-855-353-7466) or FDA at 1-800-FDA-1088 or www.fda.gov/medwatch.

FULL PRESCRIBING INFORMATION

1 INDICATIONS AND USAGE

RYPLAZIM® (plasminogen, human-tvmh) is plasma-derived human plasminogen indicated for the treatment of patients with plasminogen deficiency type 1 (hypoplasminogenemia).

2 DOSAGE AND ADMINISTRATION

For intravenous use after reconstitution only.

2.1 Dosage

Dose Determination

The recommended dosage of RYPLAZIM is 6.6 mg/kg body weight administered intravenously every 2 to 4 days (Q2D to Q4D).

Calculate the total infusion volume of RYPLAZIM using Formula (1), which is based on a final plasminogen concentration of 5.5 mg/mL. Administer the exact infusion volume determined using Formula (1) to the patient.

Formula (1): | Infusion volume (mL) = body weight (kg) × 1.2

May require more than one reconstituted vial of RYPLAZIM to obtain the infusion volume calculated using Formula (1). Round up the estimated number of vials using Formula (2).

Formula (2): | Number of vials = Infusion volume (mL) × 0.08

Determination of Dosing Frequency

1. Obtain a baseline plasminogen activity level. If the patient is receiving plasminogen supplementation with fresh frozen plasma, allow for a 7-day washout period before obtaining baseline plasminogen activity level.
2. Initiate RYPLAZIM dosing at a frequency of every three days (Q3D).
3. Obtain a trough plasminogen activity level approximately 72 hours following the initial dose of RYPLAZIM and prior to the second dose (same time of day as initial dosing)
  a. If the plasminogen activity level is < 10% [Absolute change in plasminogen activity (%)] above the baseline plasminogen level, change dosing frequency to Q2D;
  b. If the plasminogen activity level is ≥ 10 and ≤ 20% above baseline, maintain dosing frequency at Q3D;
  c. If the plasminogen activity level is > 20% above baseline, change dosing frequency to Q4D.
4. Maintain dosing frequency as determined above for 12 weeks while treating active lesions
  a. If lesions do not resolve by 12 weeks, or there are new or recurrent lesions, increase dosing frequency in one-day increments every 4-8 weeks up to Q2D dosing while reassessing clinical improvement until lesion resolution or until the lesions stabilize without further worsening. If desired clinical change does not occur by 12 weeks, check trough plasminogen activity level.
    1) If the trough plasminogen activity level is ≥ 10% above the baseline trough level, consider other treatment options, such as surgical removal of the lesion in addition to plasminogen treatment.
    2) If the trough plasminogen activity level is < 10% above the baseline trough level, obtain a second trough plasminogen activity level to confirm. If low plasminogen activity level is confirmed in combination with no clinical efficacy, consider discontinuing plasminogen treatment due to the possibility of neutralizing antibodies [see Neutralizing Antibodies (5.5)].
  b. If lesions resolve by 12 weeks, continue at same dosing frequency and monitor for new or recurrent lesions every 12 weeks.

2.2 Preparation and Reconstitution

Prepare RYPLAZIM within 3 hours of administration. Gather the following additional supplies before performing reconstitution and administration:

- One 20-mL syringe per vial of RYPLAZIM for product reconstitution
- 18- to 22-gauge needles for reconstitution and administration
- Sterile Water for Injection, USP (SWFI) (10-mL, 20-mL or 50-mL vials)
- One syringe disc filter per infusion (Baxter Supor® 5micron Syringe Filter or equivalent)
- One (or more) administration syringe(s) (20-mL, 30-mL or 60-mL)
- Alcohol wipes
- Antiseptic surface wipes
- Medical tape
- Butterfly needle or sterile infusion set
- 10 mL normal saline
- Sterile gauze pad
- Bandage

Reconstitution of RYPLAZIM

Determine the number of RYPLAZIM vials needed using Formula (2) [see Dosage and Administration (2.1)]. Check the expiration date of each vial of RYPLAZIM. Discard any expired vials. Allow RYPLAZIM vials to equilibrate to room temperature before reconstitution (at least 15 minutes if stored at 5 °C). Do not refrigerate after reconstitution.

Work on a clean surface and wash hands before performing the following procedures.

1. Remove the caps from the RYPLAZIM vials and Sterile Water for Injection, USP (SWFI) vials to expose the central portion of the rubber stoppers.
2. Sterilize the surface of the rubber stoppers with alcohol wipes and allow to dry. Do not blow on it.
3. Using a 20-mL sterile syringe with a sterile 18- to 22-gauge needle, withdraw 12.5 mL of SWFI for each vial of RYPLAZIM.
  Note: If using 10-mL vials of SWFI, each vial of RYPLAZIM requires two 10-mL vials of SWFI. Withdraw 9.0 mL of SWFI from the first 10-mL vial. Discard the first needle, attach a new 18- to 22-gauge sterile needle and withdraw 3.5 mL SWFI from the second 10-mL vial to equal 12.5 mL. Discard the used SWFI vials. Repeat this process for each vial of RYPLAZIM that needs to be reconstituted.
  If using a 20-mL or 50-mL vial of SWFI, each vial of RYPLAZIM requires only one vial of SWFI for reconstitution. Discard the used SWFI vials.
4. Using the same needle and syringe gently and slowly add the 12.5 mL of SWFI to the RYPLAZIM vial, directing the syringe down toward the side of the RYPLAZIM vial to prevent foaming. This should resemble a stream along the side of the vial (Figure 1). Discard the used syringe and needle(s).
  Figure 1
5. Gently swirl the vial by rotating it slowly to ensure that the lyophilized powder dissolves fully (Figure 2). Do not shake the vial. RYPLAZIM should fully dissolve within 10 minutes. Discard the vial if RYPLAZIM is not fully dissolved after 10 minutes.
  Figure 2
6. Observe the reconstituted vials; the solution should be colorless and clear to slightly opalescent. Discard the vial if discoloration or particulate matter are observed.
7. Repeat Steps 1 to 6 above to reconstitute each additional vial of RYPLAZIM.

Preparation of RYPLAZIM for Administration

Select an administration syringe of appropriate volume based on the infusion volume calculated using Formula (1) [see Dosage and Administration (2.1)].

Note: A 30-mL syringe can hold up to 2 vials of reconstituted RYPLAZIM and a 60-mL syringe can hold up to 4 vials of reconstituted RYPLAZIM.

Using the selected administration syringe(s) with 18- to 22-gauge needle(s), slowly withdraw the reconstituted RYPLAZIM from each vial to administer the exact infusion volume calculated using Formula (1) [see Dosage and Administration (2.1)].

Do not mix RYPLAZIM with other medications.

2.3 Administration

For intravenous use only through a syringe disc filter.

Follow the steps below for infusion:

1. One filter is needed per infusion.
2. Only administer RYPLAZIM by infusing it into a vein through a syringe disc filter.
3. Inspect the solution in the syringe. Do not use if discoloration or particulate matter are observed.
4. Administer RYPLAZIM by a separate infusion line. Do not administer RYPLAZIM with other medications.
5. Draw 10 mL of normal saline into a different syringe. Push the plunger down to remove any air bubbles.
6. Attach a syringe disc filter to the pre-filled syringe of normal saline (from previous step) and the infusion tubing with the butterfly needle. (Figure 3)
  Figure 3
7. Inject the normal saline through the syringe disc filter and butterfly needle tubing to remove any air bubbles.
8. Remove the normal saline syringe. The syringe disc filter must remain attached to the tubing, as it is required for administration of the RYPLAZIM. Discard the normal saline syringe.
9. Attach the administration syringe containing RYPLAZIM to the syringe disc filter that is connected to the butterfly needle tubing.
10. Choose a peripheral vein (e.g., antecubital or dorsum of hand). Clean the injection site with a sterile alcohol wipe and allow to dry. Do not blow on it.
11. Insert the butterfly infusion set needle in the peripheral vein, and tape in place.
12. Infuse the total dose of RYPLAZIM slowly over 10-30 minutes (approximately 5 mL/min). Using a timer (e.g., watch or clock), push the plunger of the syringe approximately 1 mL every 12 seconds. (Figure 4)
  Figure 4
13. Discard any open vials, unused solution, and administration equipment following administration.

3 DOSAGE FORMS AND STRENGTHS

RYPLAZIM is available in a single-dose 50 mL vial containing 68.8 mg of plasminogen as a lyophilized powder for reconstitution with 12.5 mL of sterile water for injection (SWFI). After reconstitution, each vial will contain 5.5 mg/mL of plasminogen in a colorless and clear to slightly opalescent solution.

4 CONTRAINDICATIONS

RYPLAZIM is contraindicated in patients with known hypersensitivity to plasminogen or other components of RYPLAZIM [See Hypersensitivity Reactions (5.4)].

5 WARNINGS AND PRECAUTIONS

5.1 Bleeding

Patients with plasminogen deficiency type 1 may bleed from active mucosal disease-related lesions during RYPLAZIM therapy. Depending on the lesion sites, this may manifest as gastrointestinal (GI) bleeding, hemoptysis, epistaxis, vaginal bleeding, or hematuria.

RYPLAZIM may worsen active bleeding not related to disease lesions. One patient with a recent history of GI bleeding due to gastric ulcers experienced GI bleeding two days after receiving the second dose of RYPLAZIM. The patient received RYPLAZIM through a compassionate use program and the dose was 6.6 mg/kg body weight every 2 days. Endoscopy showed multiple ulcers with one actively bleeding ulcer near the pylorus. Given the mechanism of action of plasminogen in fibrinolysis, it is possible that RYPLAZIM played a role in either prolonging or worsening the active bleeding. RYPLAZIM has not been studied in patients at increased risk for bleeding due to disease or injury.

Prior to initiation of treatment with RYPLAZIM, confirm healing of lesions or wounds suspected as a source of a recent bleeding event. RYPLAZIM may prolong or worsen bleeding in patients with bleeding diatheses or in patients taking anticoagulants and/or antiplatelet drugs and other agents which may interfere with normal coagulation. Monitor patients during and for 4 hours after infusion when administering RYPLAZIM to patients with bleeding diatheses and patients taking anticoagulants, antiplatelet drugs, or other agents which may interfere with normal coagulation. If a patient develops uncontrolled bleeding (defined as any gastrointestinal bleeding or bleeding from any other site that persists longer than 30 minutes), seek emergency care and discontinue RYPLAZIM immediately.

5.2 Tissue Sloughing

Tissue sloughing at mucosal sites may occur after initiation of treatment with RYPLAZIM as plasminogen activity levels are restored to physiological levels and fibrinolysis occurs. Lesions in the respiratory, gastrointestinal and genitourinary systems may slough following treatment resulting in bleeding or organ obstruction. Patients with tracheobronchial lesions may develop airway obstruction or hemoptysis. Closely monitor patients with either confirmed or suspected airway disease as manifested by cough, wheezing, shortness of breath, or changes in speech (dysphonia). Initiate the treatment with RYPLAZIM in an appropriate clinical setting with personnel trained in airway management and readily-available respiratory support equipment. Monitor at-risk patients in such a setting for a minimum of 4 hours after receiving their first dose of RYPLAZIM.

Patients with gastrointestinal and genitourinary lesions may experience tissue sloughing that causes pain, bleeding, or passage of tissue from affected organ systems. Patients should report persistent abdominal, flank, or pelvic pain to their physicians.

5.3 Transmission of Infectious Agents

Because RYPLAZIM is derived from human plasma, it carries a risk of transmitting infectious agents. Based on effective donor screening and product manufacturing processes, RYPLAZIM carries a remote risk for transmission of viral diseases and variant Creutzfeldt-Jakob disease (vCJD). There is a theoretical risk for transmission of Creutzfeldt-Jakob disease (CJD), but if that risk actually exists, the risk of transmission would also be considered extremely low. It is also possible that unknown infectious agents may be present in RYPLAZIM. The risk of infectious agent transmission has been reduced by screening plasma donors for prior exposure to certain viruses, testing for the presence of certain current virus infections, and including virus inactivation/removal steps in the manufacturing process for RYPLAZIM [see Description (11)].

Report any infection thought to be possibly transmitted by RYPLAZIM to Kedrion Biopharma, Inc. at 1-855-3KDRION (1-855-353-7466) or FDA at 1-800-FDA-1088 or www.fda.gov/medwatch.

5.4 Hypersensitivity Reactions

Hypersensitivity reactions, including anaphylaxis, may occur with RYPLAZIM [see Contraindications (4)]. In case of a hypersensitivity reaction, discontinue RYPLAZIM immediately and treat according to standard medical practice.

5.5 Neutralizing Antibodies

Formation of neutralizing antibodies (inhibitors) to plasminogen following the administration of RYPLAZIM has not been reported to date [See Immunogenicity (6.2)]. Monitor patients for the loss of clinical efficacy as manifested by the development of new or recurrent lesions while on RYPLAZIM therapy, and obtain plasminogen activity trough levels to confirm that adequate plasminogen activity levels have been achieved and are being maintained [see Dosage and Administration (2)].

5.6 Laboratory Abnormalities

Patients receiving RYPLAZIM may have elevated levels of D-dimer in blood. Interpret D-dimer levels with caution in patients being screened for venous thromboembolism (VTE), as elevated levels may be associated with the physiological activity of RYPLAZIM (fibrinolysis of ligneous lesions) and not indicative of VTE. Consider other tests to screen for VTE in patients receiving RYPLAZIM, as D-dimer levels will lack interpretability.

6 ADVERSE REACTIONS

The most frequent (incidence ≥ 10%) adverse reactions were abdominal pain, bloating, nausea, fatigue, extremity pain, hemorrhage, constipation, dry mouth, headache, dizziness, arthralgia, and back pain.

6.1 Clinical Trials Experience

As clinical trials are conducted under widely varying conditions, adverse reaction rates observed in the clinical trials of a drug cannot be directly compared to rates in the clinical trials of another drug and may not reflect the rates observed in clinical practice.

The safety data described in this section reflect exposure to RYPLAZIM in two single-arm, open-label clinical trials as well as expanded access and compassionate use programs for a total of 29 patients with plasminogen deficiency type 1 who received at least one dose of RYPLAZIM. Patients were between 11 months and 42 years of age. There were 18 pediatric patients and 11 adult patients. Fifteen patients were female. Twenty-eight patients were Caucasian, and one patient was Asian.

RYPLAZIM Trial 1 enrolled 7 patients (5 female) of whom 2 were pediatric patients (age 13 to 15 years) and 5 were adults. Five patients received two infusions: one 2 mg/kg infusion, and one 6 mg/kg infusion. Two patients received a single 6 mg/kg infusion. There were no adverse reactions in this trial.

RYPLAZIM Trial 2 enrolled 15 patients (11 female) of whom 6 were pediatric patients (age 4 to 16 years) and 9 were adults. Six of the 15 patients participated in RYPLAZIM Trial 1. Treatment duration ranged from 48 to 124 weeks. All patients received RYPLAZIM at a dose of 6.6 mg/kg administered every second, third or fourth day for 48 weeks.

A long-term treatment protocol enrolled 12 patients (8 female) of whom 8 were pediatric patients (age 16 months to 16 years) and 4 were adults. Eight patients in this treatment protocol continued from Trial 2 and 4 patients were from individual expanded access protocols in the US. All 12 patients continue to receive RYPLAZIM at the dose of 6.6 mg/kg every 2 to 4 days.

Fourteen patients (5 female) received RYPLAZIM through expanded access programs. There were 8 pediatric patients (age 11 months to 17 years) and 6 adults. Patients' dosage regimens were adjusted based on clinical response, and the regimens varied between 6.6 mg/kg every 1 to 7 days.

Table 1 shows the most frequent adverse reactions (incidence ≥ 10%) observed in the two trials and in the treatment protocols.

Table 1 Adverse Reactions Reported in ≥ 10% of Patients with Plasminogen Deficiency Type 1 (N=19 [Age range of patients: 16 months to 42 years. 9 patients who received RYPLAZIM through single-patient expanded access were not included in the total population for the determination of adverse reaction frequency because their safety data were not as rigorously collected as patients in the clinical trials. Also not included is one patient from trial 1 who only received a single dose.])
Adverse Reactions | Number of Patients (%)(N = 19)
Abdominal pain | 3 (16%)
Gastric dilatation (bloating/feel bloated) | 3 (16%)
Nausea | 3 (16%)
Fatigue | 3 (16%)
Pain in extremity | 3 (16%)
Hemorrhage | 3 (16%)
Constipation | 2 (11%)
Dry mouth | 2 (11%)
Headache | 2 (11%)
Dizziness | 2 (11%)
Arthralgia | 2 (11%)
Back pain | 2 (11%)

6.2 Immunogenicity

In RYPLAZIM Trial 2, three patients (20%) developed anti-plasminogen antibodies following RYPLAZIM treatment. Comparison of pharmacokinetic (PK) parameters and /or trough activity levels for those positive samples with the parameters assessed either at baseline or for negative samples suggest these antibodies are not neutralizing antibodies (inhibitors) to plasminogen.

The detection of anti-plasminogen antibodies depends on the sensitivity and specificity of the test methods used. Additionally, the observed incidence of antibody positivity in a test method may be influenced by several factors, including sample handling, timing of sample collection, drug interference, concomitant medication, and the underlying disease. For these reasons, comparison of the incidence of antibodies to RYPLAZIM with the incidence of antibodies to other products may be misleading.

8 USE IN SPECIFIC POPULATIONS

8.1 Pregnancy

Risk Summary

There are no clinical trials of RYPLAZIM use in pregnant women. No animal reproductive and developmental toxicity studies have been conducted with RYPLAZIM to assess whether it can cause fetal harm when administered to a pregnant woman. In the United States, the background risk of major birth defects is about 3%, and miscarriage occurs in up to 20% of clinically-recognized pregnancies.

8.2 Lactation

Risk Summary

Endogenous plasminogen is excreted in human milk; however, there is no information available on the presence of RYPLAZIM in human milk, the effects on the breastfed infant, or the effects on milk production. The developmental and health benefits of breastfeeding should be considered along with the mother's clinical need for RYPLAZIM and any potential adverse effects on the breastfed infant from RYPLAZIM or from the underlying maternal condition.

8.4 Pediatric Use

The safety and efficacy of RYPLAZIM has been established in pediatric patients. Use of RYPLAZIM is supported by the two clinical trials, and expanded access and compassionate use programs that included 18 pediatric patients age 11 months to 17 years [see Clinical Studies (14), and Adverse Reactions (6)].

8.5 Geriatric Use

The safety and effectiveness of RYPLAZIM have not been established in geriatric patients. Clinical studies of RYPLAZIM for this indication did not include patients age 65 years and over. In general, dose selection for an elderly patient should be cautious, usually starting at the low end of the dosing range, reflecting the greater frequency of decreased hepatic, renal, or cardiac function, and of concomitant disease or other drug therapy.

11 DESCRIPTION

RYPLAZIM is a Glu-plasminogen (> 95% purity) which is the native circulating form of plasminogen in the blood. RYPLAZIM is a sterile, white to off-white, lyophilized preparation of purified, plasma-derived plasminogen (human) to be reconstituted and administered by the intravenous route. Each vial of RYPLAZIM contains 68.8 mg of plasminogen. Following reconstitution with 12.5 mL of sterile water for injection (SWFI), the RYPLAZIM solution contains 5.5 mg/mL plasminogen and the following inactive ingredients: sodium citrate, sodium chloride, glycine, and sucrose. RYPLAZIM contains no preservatives. Biological potency of the plasminogen is determined by a chromogenic assay calibrated with a standard.

All plasma used in the manufacturing of RYPLAZIM is tested using serological assays for hepatitis B virus (HBV) surface antigen and antibodies to human immunodeficiency virus-1/2 (HIV-1/2) and hepatitis C virus (HCV). The plasma is also tested via nucleic acid amplification testing for HBV, HCV, HIV-1, hepatitis A virus (HAV) and human parvovirus B19 virus. Only plasma pools negative for HIV-1, HCV, HBV, and HAV, and containing levels of human parvovirus B19 DNA ≤ 10^4 IU/mL are used for the manufacture of RYPLAZIM.

The RYPLAZIM manufacturing process encompasses a series of chromatography adsorbents to purify plasminogen and includes multiple steps and controls to ensure that the purified plasminogen is essentially free of known adventitious agents. First, three orthogonal viral removal/inactivation steps are included: affinity chromatography for removal of enveloped and non-enveloped viruses; solvent/detergent treatment for inactivation of enveloped viruses; and 20 nm nanofiltration for removal of both enveloped and non-enveloped viruses. Two independent studies demonstrated effective viral removal/inactivation afforded by these three steps using validated scaled-down models. The overall virus reduction achieved in these studies for enveloped viruses was ≥ 11.8 logs and for non-enveloped viruses was ≥ 9.7 logs (considering both contributing steps), as summarized in Table 2. Second, the plasma used in this process is Human Source Plasma from FDA-approved collection centers; thus, there is minimal risk of contamination that could cause transmissible spongiform encephalopathies. Lastly, the product is tested for microbial and endotoxin levels throughout the process.

Table 2: Viral Clearance Capacity of the Manufacturing Process
 | Enveloped Viruses |  |  | Non EnvelopedViruses
Process Step | HIV-1 | BVDV | PRV | HAV | PPV | Reo-3 | EMCV
Affinity chromatography | ≥ 5.22 | ND [ND: Not determined;] | ND | 3.64 | 2.64 | ND | 3.55
Solvent/Detergent treatment | > 6.09 | > 5.77 | > 6.54 | NA [NA: Not Applicable; LRV: Log reduction value; BVDV = Bovine viral diarrhea virus; EMCV = Encephalomyocarditis virus; HAV = Hepatitis A virus; HIV-1 = Human immunodeficiency virus type 1; PPV = Porcine parvovirus; PRV = Pseudorabies virus; Reo-3 = Reovirus Type 3] | NA | NA | NA
Nanofiltration | > 5.89 | > 6.02 | > 6.51 | > 7.08 | > 7.03 | > 7.08 | ND
Total LRV | ≥ 17.2 | ≥ 11.8 | ≥ 13.1 | ≥ 10.7 | ≥ 9.7 | ≥ 7.1 | 3.6

12 CLINICAL PHARMACOLOGY

12.1 Mechanism of Action

Treatment with RYPLAZIM temporarily increases plasminogen levels in blood.

12.2 Pharmacodynamics

Plasminogen deficiency type 1 is characterized by decreased plasminogen levels that causes formation of fibrin-rich, ligneous pseudomembranous lesions on mucous membranes that can impair normal tissue and organ function. Replacement therapy increases the plasma level of plasminogen enabling a temporary correction of the plasminogen deficiency and reduction or resolution of extravascular fibrinous lesions.

12.3 Pharmacokinetics

The pharmacokinetics of RYPLAZIM were assessed by plasminogen activity (chromogenic assay) in plasma. Plasminogen was measured as both absolute and baseline-adjustedlevels.

In RYPLAZIM Trial 2, pharmacokinetic analyses were conducted in 15 patients (9 adults) who completed at least 12 weeks of RYPLAZIM 6.6 mg/kg administered every second, third or fourth day and had sufficient plasma samples. Full pharmacokinetic profiles of plasminogen were measured over 96 hours after the first and Week 12 infusions, and trough levels of plasminogen were measured at baseline and at Weeks 2, 4, 6, 8, 10, and 12.

Mean absolute plasminogen activity in adult and pediatric patients reached physiological levels (70% to 130%) immediately after the first infusion, were sustained for approximately 24 hours, and remained an absolute 10% above baseline 72 hours after dosing. After 12 weeks, mean absolute plasminogen activity in adult and pediatric patients reached physiological levels (70% to 130%) immediately after dosing, were sustained for approximately 24 hours, and continued to maintain an absolute 10% above baseline 96 hours after dosing.

Although some inter-patient variability was observed, PK parameters for baseline-adjusted plasminogen activity levels were generally similar between adult and pediatric patients.

Table 3: Mean (± Standard Deviation) Pharmacokinetic Parameters of Baseline-Adjusted [Baseline-adjusted plasminogen activity levels were calculated by subtracting the baseline (pre-infusion) value from each subsequent time-point. Note: plasminogen activity levels measured with a chromogenic assay.] Plasminogen Activity Levels in Adult and Pediatric Patients After the First Dose and 12 Weeks RYPLAZIM
PK Parameter | First Dose Adult (N=9) | Week 12 Adult (N=9) | First Dose Pediatric (N=6) | Week 12 Pediatric (N=6) | First Dose Total (N=15) | Week 12 Total (N=15)
AUCLast (hr*%) | 2860.9 (700.7) | 4665.6 (762.1) | 3367.6 (852.8) | 4641.6 (1393.4) | 3063.6 (778.7) | 4656.0 (1012.7)
AUCInf (hr*%) | 3317.3 (915.7) | 5676.0 (1186.6) | 4038.5 (1104.2) | 5815.5 (1863.5) | 3605.8 (1023.9) | 5731.8 (1431.7)
CL (mL/h/kg) | 1.5 (0.5) | 0.9 (0.2) | 1.3 (0.4) | 0.9 (0.3) | 1.4 (0.5) | 0.9 (0.3)
Cmax (%) | 90.9 (17.5) | 127.4 (17.4) | 102.0 (31.1) | 120.3 (31.6) | 95.3 (23.5) | 124.6 (23.3)
MRTLast (hr) | 29.7 (3.7) | 33.0 (1.6) | 31.8 (2.0) | 34.2 (1.5) | 30.6 (3.2) | 33.5 (1.6)
Vss (mL/kg) | 62.8 (11.2) | 47.2 (5.6) | 64.1 (12.9) | 52.5 (15.2) | 63.3 (11.4) | 49.3 (10.4)
T1/2 (hr) | 32.4 (13.1) | 38.5 (7.1) | 36.3 (10.0) | 40.3 (5.0) | 34.0 (11.7) | 39.2 (6.2)
AUCLast = area under the time-concentration curve, from time 0 to the last measured time point; AUCInf = extrapolated area under the time-concentration curve, from time 0 to infinity; CL = clearance; Cmax = peak concentration; MRTLast = mean residence time from time 0 to the last measured time point; Vss = steady-state volume of distribution; T1/2 = half-life

Table 4 : Mean (± Standard Deviation) Plasminogen Activity Trough Levels in Adult and Pediatric Patients Through 12 Weeks of RYPLAZIM dosing.
Study Population | Baseline | Week 2 | Week 4 | Week 6 | Week 8 | Week 10 | Week 12
Adult (N = 9) | 20.3 (13.7) | 44.7 (18.6) | 50.8 (17.1) | 55.4 (12.0) | 50.3 (19.5) | 51.1 (15.5) | 51.7 (12.3)
Pediatric (N = 6) | 22.3 (5.1) | 47.7 (7.4) | 46.2 (10.5) | 47.8 (9.8) | 45.2 (14.8) | 48.8 (6.4) | 50.0 (12 6)
Combined (N = 15) | 21.1 (10.8) | 45.9 (14.8) | 48.9 (14.6) | 52.4 (11.5) | 48.3 (17.4) | 50.2 (12.4) | 51.0 (12.0)
Plasminogen activity levels measured with a chromogenic assay. Normal range: 70%-130%, as determined by the laboratory.
Individual plasminogen activity values reported as < 5% were set at 5% for mean calculation.
There was no Week 2 plasminogen activity trough value for one adult patient; however, an unscheduled Week 3 value was obtained and used for mean calculation. Baseline value corresponds to endogenous plasminogen level.

13 NONCLINICAL TOXICOLOGY

13.1 Carcinogenesis, Mutagenesis, Impairment of Fertility

No animal studies have been conducted to evaluate the effect of RYPLAZIM on carcinogenesis, mutagenesis, or impairment of fertility.

13.2 Animal Toxicology and/or Pharmacology

No toxicity was observed in healthy rats following intravenous administration of RYPLAZIM at dose levels of 1.2, 7.3, and 21.8 mg/kg/day for 5 consecutive days.

14 CLINICAL STUDIES

The efficacy of RYPLAZIM in pediatric and adult patients with plasminogen deficiency type 1 was evaluated in a single-arm, open-label clinical trial (RYPLAZIM Trial 2). A total of 15 patients with plasminogen deficiency type 1 were enrolled. All patients had a baseline plasminogen activity level between <5% and 45% of normal, and biallelic mutations in the plasminogen (PLG) gene. The age range of these patients was 4 to 42 years, including 6 pediatric patients age 4 to 16 years, and 9 adults. Eleven patients were female. All patients were White. All patients received RYPLAZIM at a dose of 6.6 mg/kg administered every 2 to 4 days for 48 weeks to achieve at least an increase of individual trough plasminogen activity by an absolute 10% above baseline and to treat the clinical manifestations of the disease.

Efficacy was established on the basis of overall rate of clinical success at 48 weeks. Overall rate of clinical success is defined as 50% of patients with visible or other measurable non-visible lesions achieving at least 50% improvement in lesion number/size, or functionality impact from baseline. Spirometry was the only test of organ function used and one patient had abnormal spirometry at baseline. This patient had a history of ligneous airway disease with a severe obstructive ventilatory defect (FEV1: 46.7% of predicted normal) at baseline prior to treatment that corrected to normal (FEV1: 89.3% of predicted normal) after 12 weeks of treatment. All patients with any lesion at baseline had at least 50% improvement in the number/size of their lesions.

External Lesions: Twenty-five of the 32 (78%) external lesions [with sites mainly located in the eyes (ligneous conjunctivitis), nose, gums (ligneous gingivitis), ligneous lesions of the hands and feet] were resolved by the end of Week 48. There were no recurrent or new external lesions in any patient through Week 48.

Internal Lesions: Nine of the 12 (75%) assessed internal lesions were resolved by Week 48. The lesion sites were mainly located in the cervix, bronchus, colon, vagina and uterus. No recurrent or new lesions were found on imaging in any patient through Week 48.

16 HOW SUPPLIED/STORAGE AND HANDLING

RYPLAZIM is supplied in a single-dose vial [NDC 70573-099-01] containing 68.8 mg of plasminogen (human) (5.5 mg/mL after reconstitution with 12.5 mL of SWFI), one vial per carton [NDC 70573-099-02]. The treating physician will provide reconstitution and administration supplies. RYPLAZIM contains no preservatives.

STORAGE AND HANDLING

- Store RYPLAZIM at temperatures of 2°C to 25°C (36°F to 77°F) in its original carton until ready to use. Do not freeze.
- Once reconstituted, RYPLAZIM must be administered within 3 hours. Do not refrigerate after reconstitution.
- Store diluent and syringe disc filters at 20°C to 25°C (68°F to 77°F).
- Do not use RYPLAZIM or diluent after the expiration date on the carton and vial labels.

17 PATIENT COUNSELING INFORMATION

- Advise patients and/or caregiver to read the FDA-approved patient labeling (Patient Information and Instructions for Use).
- Counsel patients and/or caregiver to discontinue RYPLAZIM and immediately contact their physicians if signs or symptoms of a possible hypersensitivity reaction occur, such as hives, generalized urticaria, angioedema, chest tightness, wheezing, tachycardia, and hypotension [see Contraindications (4)], Warnings and Precautions (5.4)].
- Inform patients that bleeding from active mucosal disease-related lesions and worsening of active bleeding not related to those lesions during RYPLAZIM therapy may occur. Depending on the lesion sites, this may manifest as gastrointestinal bleeding, hemoptysis, epistaxis, vaginal bleeding, or hematuria. Prior to initiation of treatment with RYPLAZIM, lesions or wounds suspected as the source of recent bleeding events should be confirmed to have healed. RYPLAZIM may prolong or worsen bleeding in patients with bleeding diatheses and/or taking anticoagulants or antiplatelet drugs. If a patient develops serious bleeding, seek emergency care and discontinue RYPLAZIM immediately [see Warnings and Precautions (5.1)].
- Inform patients that tissue sloughing at mucosal sites may occur at initiation of RYPLAZIM therapy as lesions resolve. Patients with respiratory lesion are at risk for respiratory compromise and initial treatment with RYPLAZIM should be performed in a clinical setting with close monitoring. Patients with lesions in gastrointestinal and genitourinary systems may experience tissue sloughing that may cause pain, mucosal bleeding, or passage of tissue referable to those organ systems. Patients should report persistent abdominal, flank or pelvic pain to their physicians if not resolved. [see Warnings and Precautions (5.2)].
- Inform patients and/or caregiver that RYPLAZIM is made from human plasma and may contain infectious agents that can cause disease (eg, viruses, the variant Creutzfeldt-Jakob disease [vCJD] agent and, theoretically the CJD agent). Explain that the risk that RYPLAZIM may transmit an infectious agent has been reduced by screening the plasma donors, by testing donated plasma for certain virus infections, and by inactivating or removing certain viruses during manufacturing. Counsel patients and/or caregiver to report any symptoms that concern them. [see Warnings and Precautions (5.3)].
- Advise patients and/or caregivers that antibodies may develop during treatment that make RYPLAZIM less effective [see Warnings and Precautions (5.5)].
- Advise female patients who are pregnant or may become pregnant that the potential effects of RYPLAZIM on pregnancy and breastfeeding are unknown. They should notify their physicians if they become or intend to become pregnant, or if they plan to breastfeed. [see Use in Special Populations (8.1) and (8.2)].
- Self-administration: ensure patient/caregiver has received detailed instructions and training and has shown the ability to safely and independently administer RYPLAZIM.

Manufactured by:
Prometic Bioproduction, Inc
531 Blvd. des Prairies, Building 15
Laval, Quebec, Canada, H7V1B7

Manufactured for:
Kedrion Biopharma, Inc.
Parker Plaza, 400 Kelby Street, 11th floor,
Fort Lee, NJ, 07024
United States
U.S. License number 1906

PATIENT INFORMATION

RYPLAZIM®
plasminogen, human-tvmh

The following summarizes important information that you should read carefully before using RYPLAZIM (pronounced ri plaz' im). This does not replace talking with your healthcare provider, and it does not include all of the important information about RYPLAZIM. If you have any questions after reading this information, then ask your healthcare provider.

What is RYPLAZIM?

RYPLAZIM is a medicine containing human plasminogen and is used to increase the blood levels of plasminogen in people with plasminogen deficiency type 1 (hypoplasminogenemia). It is injected into a vein.

Who should not use RYPLAZIM?

Do not take RYPLAZIM if you have had a severe reaction to RYPLAZIM or another product containing plasminogen.

What should I tell my healthcare provider before using RYPLAZIM?

Before taking RYPLAZIM, tell your healthcare provider if you:

- Have had other medical problems, particularly bleeding problems.
- Use any medicine, including prescription and over-the-counter drugs, supplements, and herbal remedies.
- Have had reactions to any medications.
- Are pregnant or planning to become pregnant. It is not known whether RYPLAZIM may affect your pregnancy or an unborn baby.
- Are breastfeeding or are planning to breastfeed. It is not known whether RYPLAZIM affects milk production, passes into breast milk and may affect a baby.

How do I take RYPLAZIM?

- RYPLAZIM is given directly into the bloodstream.
- You may receive RYPLAZIM at a healthcare facility, or you may receive it at home from a nurse, caregiver or by injecting it yourself. If your healthcare provider believes you would be able to inject RYPLAZIM yourself or with the help of others at home, then you will receive detailed instructions and training on preparation and infusion (see Instructions for Use at the end of this document).
- Your healthcare provider will tell you how often to take RYPLAZIM and how much RYPLAZIM to use each time.
- Your healthcare provider may order periodic blood tests to check your plasminogen level.

What are the possible or reasonably likely side effects of RYPLAZIM?

- Common side effects of RYPLAZIM are:
  - abdominal pain
  - bloating
  - nausea
  - fatigue
  - extremity pain
  - hemorrhage
  - constipation
  - dry mouth
  - headache
  - dizziness
  - joint pain
  - back pain
- You may have an allergic reaction while taking RYPLAZIM. Stop treatment and contact your healthcare provider immediately if you develop trouble breathing, wheezing, chest tightness, light headedness, dizziness, swelling in the face or throat, itching, a rash, or hives.
- Your body may make antibodies against RYPLAZIM that may stop RYPLAZIM from working properly. Your healthcare provider will monitor you periodically for lesions which may be due to a low plasminogen level. If you develop new lesions or a recurrence of a previous lesion, then your healthcare provider will obtain blood to test for plasminogen activity level.
- RYPLAZIM may worsen or prolong ongoing bleeding. In addition, if you have abnormal tissue growths because of your low plasminogen level, then you may have bleeding as these growths heal in response to treatment with RYPLAZIM.
  - If you vomit blood, have blood from your rectum or black tarry stools or any bleeding that is heavy or does not resolve after 30 minutes of direct pressure seek emergency care and discontinue further use of RYPLAZIM.
- As your lesions heal then they will fall off, known as tissue sloughing, this is in response to treatment with RYPLAZIM. This is also normal response and is not a side effect. Specific examples:
  - If you have tissue growths in your airway or lungs you may cough up small amounts of tissue and you may cough up a small amount of blood or blood clots.
  - If you have tissue growths in your genitourinary system then you may pass tissue or blood clots in your urine or from your penis or vagina.
  - If you have tissue growths in your gastrointestinal system you may have some tissue or blood clots in your stool or you may vomit blood or blood clots.
  - If you have eye lesions you may have oozing of blood from the lesions in your eye.
  - Notify your healthcare provider if you develop breathing difficulty, wheezing, cough, changes in speech, or pain in the back, abdomen, groin, or pelvic area, because these could be symptoms of tissue from resolving lesions that are obstructing the lungs, the kidneys, the bladder, the uterus and/or vagina, or the intestines.
- Other side effects are possible. Speak with your healthcare provider about any side effects that do not go away or bother you.

You may report side effects to Kedrion Biopharma, Inc. at 1 855-353-7466 or to FDA at 1-800-FDA-1088 or www.fda.gov/medwatch.

How do I store RYPLAZIM?

- Store RYPLAZIM vials in the refrigerator or at room temperature (36°F to 77°F, [2°C to 25°C]). Do not freeze.
- Store the other supplies at room temperature (68°F to 77°F [20°C to 25°C]).
- After the RYPLAZIM vials are opened and mixed with Sterile Water for Injection (SWFI), they must be used within 3 hours.
- Keep the RYPLAZIM vials in the original package before using.
- Do not use RYPLAZIM or SWFI after the expiration date on the vials.

Do not use RYPLAZIM for a condition other than that prescribed by your healthcare provider.

Do not share RYPLAZIM with other people, even if they have the same symptoms that you have.

RYPLAZIM® plasminogen, human-tvmh Instructions for Use

For intravenous use after reconstitution only

Do not attempt an intravenous infusion on yourself unless you or your caregiver has been trained by a healthcare provider. Always follow the specific instructions that your healthcare provider has given you. The steps listed below are general guidelines for using RYPLAZIM. If you are unsure about any of the steps, contact your healthcare provider before using.

A. Gathering Supplies
  1. Your healthcare provider should tell you how many vials of RYPLAZIM to use based on your weight. If you store RYPLAZIM in the refrigerator, then let the vials sit at room temperature for at least 15 minutes before you use them.
  2. Check the expiration date on the vial labels and carton. Do not use RYPLAZIM or Sterile Water for Injection, USP vials after the expiration date.
  3. Make sure you work on a clean, flat surface.
  4. Gather the following supplies and any other materials that you will need, as instructed by your healthcare provider:
    - Required number of vials of RYPLAZIM
    - One 20-mL syringe per vial of RYPLAZIM for mixing the drug
    - 18- to 22-gauge needles for reconstitution and administration
    - Sterile Water for Injection, USP (SWFI) (10 mL, 20 mL or 50 mL)
    - One syringe disc filter per infusion of RYPLAZIM required (Baxter Supor® 5-micron Syringe Filter or equivalent)
    - One (or more) administration syringe(s) (20mL, 30mL or 60 mL)
    - Alcohol wipes
    - Antiseptic surface wipes
    - Medical tape
    - Butterfly needle or sterile infusion set
    - 10 mL normal saline
    - Sterile gauze pad
    - Bandage
B. Preparing RYPLAZIM
  1. Always work on a clean surface and wash your hands before performing the procedure.
  2. Once the RYPLAZIM has been prepared, use it at room temperature within 3 hours. Do not refrigerate after preparation.
  3. Remove the caps from the RYPLAZIM vials and the Sterile Water for Injection, USP (SWFI) vials to expose the central portion of the rubber stoppers.
  4. Clean the surface of the rubber stoppers with alcohol wipes and allow to dry. Do not blow on them. Do not touch the rubber stoppers with your hand after cleaning them.
  5. Using a syringe with an 18- to 22-gauge needle, draw 12.5 mL of SWFI. Ensure that all air bubbles have been removed.
    Note: Depending on the SWFI vial sizes used, more than one SWFI vial(s) may be required.
    - If using a 10-mL vial of SWFI, you will need two 10-mL vials of SWFI for each vial of RYPLAZIM. Draw 9.0 mL of SWFI from the first SWFI vial with the 20-mL syringe. Discard the first needle, attach a new 18- to 22-gauge sterile needle and draw 3.5 mL from the second 10-mL vial of SWFI to equal to 12.5 mL.
    - Repeat the above process for every vial of RYPLAZIM that will need to be reconstituted.
    - If using a 20-mL or 50-mL vial of SWFI, only one vial of SWFI per vial of RYPLAZIM will be needed for reconstitution.
    - Do not use the remaining SWFI in the vial with a different RYPLAZIM vial.
  6. Gently and slowly add the 12.5 mL of SWFI down the side of the RYPLAZIM vial to prevent foaming. This should resemble a stream down the side of the vial. (Fig. A). Discard used syringe and needle(s).
    Fig. A
  7. Gently swirl the RYPLAZIM vial in slow rotation to ensure it is fully dissolved. Do not shake the vial. The RYPLAZIM should fully dissolve within 10 minutes. Discard if the product is not fully dissolved after 10 minutes. (Fig B)
    Fig. B
  8. After the RYPLAZIM is dissolved in the SWFI, inspect the solution. It should be colorless and clear to slightly pearly. Discard if discoloration or particulate matter is observed.
  9. Repeat Preparation Steps 3 to 8 above for each vial of RYPLAZIM needed.
  10. Select an administration syringe of appropriate volume based on the dose required. Depending on the syringe size used, more than one vial of mixed RYPLAZIM can be drawn into one administration syringe.
    NOTE: A 30-mL syringe cannot hold more than 2 vials of reconstituted RYPLAZIM and a 60-mL syringe cannot hold more than 4 vials of reconstituted RYPLAZIM.
  11. Using the selected administration syringe(s) with an 18- to 22-gauge needle, slowly draw the RYPLAZIM from each reconstituted vial to administer the required dose of RYPLAZIM. Do not mix RYPLAZIM with other medications.
  12. After drawing the RYPLAZIM from the last vial, push the plunger down to remove any air bubbles. Dispose of the needle in an appropriate container.

Infusing RYPLAZIM

1. One filter is needed per infusion.
2. Only administer RYPLAZIM by infusing it into a vein through a syringe disc filter.
3. Inspect the solution in the syringe. Do not use if you see discoloration or particulate matter.
4. Administer RYPLAZIM by a separate infusion line. Do not administer RYPLAZIM with other medications.
5. Draw 10 mL of normal saline into a different syringe. Push the plunger down to remove any air bubbles.
6. Attach a syringe disc filter to the pre-filled syringe of normal saline (from previous step) and the infusion tubing with butterfly needle. (Fig. C)
  Fig. C
7. Inject the normal saline through the syringe disc filter and butterfly needle tubing to remove any air bubbles.
8. Remove the normal saline syringe. The syringe disc filter must remain attached to the tubing, as it is required for administration of the RYPLAZIM. Discard the normal saline syringe.
9. Attach the administration syringe containing RYPLAZIM to the syringe disc filter that is connected to the butterfly needle tubing.
10. Choose a peripheral vein (e.g., antecubital or dorsum of hand). Clean the injection site with a sterile alcohol wipe and allow to dry. Do not blow on it.
11. Insert the butterfly infusion set needle in the chosen peripheral vein, as taught by your healthcare provider, and tape in place.
12. Infuse the amount of RYPLAZIM you need as instructed by your healthcare provider. Deliver the total dose slowly over 10-30 minutes (approximately 5 mL/min). Using a timer (e.g., watch or clock), push the plunger of the syringe approximately 1 mL every 12 seconds. (Fig. D)
  Fig. D
13. Discard any open vials, unused solution, and administration equipment following administration.

Manufactured by:
Prometic Bioproduction Inc
531 Blvd. des Prairies,
Laval, Quebec, Canada, H7V1B7

Manufactured for:
Kedrion Biopharma, Inc.
Parker Plaza, 400 Kelby Street, 11th floor,
Fort Lee, NJ, 07024
United States
U.S. License number 1906

PRINCIPAL DISPLAY PANEL - 68.8 mg Vial Label

NDC 70573-099-01

68.8 mg/vial

plasminogen, human-tvmh
Ryplazim®

For Intravenous Use Only
Sterile, Preservative-Free
Single-Dose Vial
Discard Unused Portion

US LIC. NO.: 1906
Rx Only

PRINCIPAL DISPLAY PANEL - 68.8 mg Vial Carton

68.8 mg/vial

plasminogen, human-tvmh
Ryplazim®

For Intravenous Use Only
Sterile, Preservative-Free
Single-Dose Vial
Discard Unused Portion

US LIC NO.: 1906
Rx Only